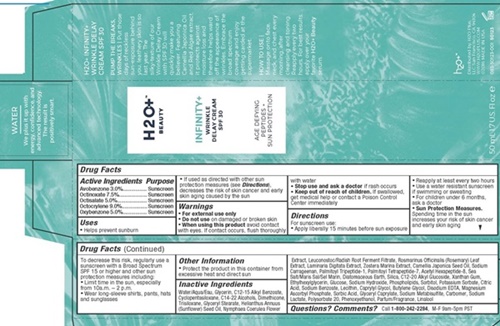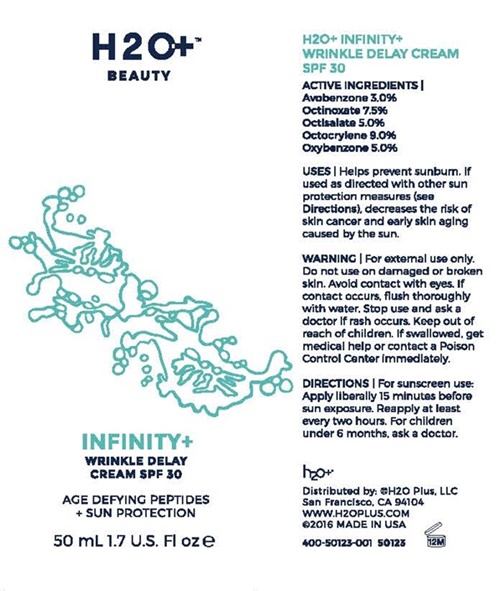 DRUG LABEL: INFINITY
NDC: 54111-130 | Form: CREAM
Manufacturer: Bentley Laboratories, LLC
Category: otc | Type: HUMAN OTC DRUG LABEL
Date: 20181219

ACTIVE INGREDIENTS: AVOBENZONE 1.5 g/50 mL; OCTINOXATE 3.75 g/50 mL; OCTISALATE 2.5 g/50 mL; OXYBENZONE 2.5 g/50 mL; OCTOCRYLENE 4.5 g/50 mL
INACTIVE INGREDIENTS: WATER; ALKYL (C12-15) BENZOATE; CYCLOMETHICONE 5; C14-22 ALCOHOLS; DIMETHICONE; TRISILOXANE; GLYCERYL MONOSTEARATE; SUNFLOWER OIL; NYMPHAEA CAERULEA FLOWER; LEUCONOSTOC/RADISH ROOT FERMENT FILTRATE; ROSEMARY; LAMINARIA DIGITATA; ZOSTERA MARINA SEED; CAMELLIA JAPONICA SEED OIL; CARRAGEENAN SODIUM; PALMITOYL TRIPEPTIDE-1; PALMITOYL TETRAPEPTIDE-7; ACETYL HEXAPEPTIDE-8; SEA SALT; DIATOMACEOUS EARTH; CALCIUM ALUMINOSILICATE; SILICON DIOXIDE; C12-20 ALKYL GLUCOSIDE; XANTHAN GUM; ETHYLHEXYLGLYCERIN; DEXTROSE, UNSPECIFIED FORM; SODIUM HYDROXIDE; LECITHIN, SOYBEAN; SORBITOL; POTASSIUM SORBATE; CITRIC ACID MONOHYDRATE; SODIUM BENZOATE; CAPRYLYL GLYCOL; BUTYLENE GLYCOL; EDETATE DISODIUM; MAGNESIUM ASCORBYL PHOSPHATE; SORBIC ACID; GLYCERYL CAPRYLATE; SODIUM METABISULFITE; CARBOXYPOLYMETHYLENE; SODIUM LACTATE; POLYSORBATE 20; PHENOXYETHANOL; LINALOOL, (+/-)-

Infinity + Wrinkle Delay Cream SPF 30 - 130

Drug Facts Active Ingredients

Avobenzone 3.0%

Octinoxare 7.5%

Octisalate 5.0%

Octocrylene 9.0%

Oxybenzone 5.0%

Purpose

Sunscreen

Keep out of reach of children

- If swallowed, get medical help or contact a Poison Control Center immediately.

Uses

- Helps prevent sunburn
- If used as directed with other sun protection measures (see Directions), decreases the risk of skin cancer and early skin aging caused by the sun

Warnings

For external use only

Do not use

on damaged or broken skin

When using this product

avoid contact with eyes. If contact occurs, flush thoroughly with water

Stop use and ask a doctor

if rash occursf rash occurs

Directions

For sunscreen use:

- Apply liberally 15 minutes before sun exposure
- Reapply at least every two hours
- Use a water resistant sunscreen if swimming or sweating
- For children under 6 months, ask a doctor

Sun Protection Measures.

Spending time in the sun increases your risk of skin cancer and early skin aging. To decrease this risk, regularly use a sunscreen with a Broad Spectrum SPF 15 or higher and other sun protection measures including:

- Limit time in the sun, especially from 10 a.m. - 2 p.m.
- Wear long-sleeve shirts, pants, hats and sunglasses

Other Information

- Protect the product in this container from excessive heat and direct sun

Inactive Ingredients

Water/Aqua/Eau, C12-15 Alkyl Benzoate, Glycerin, Cyclopentasiloxane, C14-22 Alcohols, Trisiloxane, Dimethicone, Glyceryl Stearate, Helianthus Annuus (Sunflower) Seed Oil, Nymphaes Coerulea Flower Extract, Leuconostoc/Radish Root Ferment Filtrate, Rosmarinus Officinalis (Rosemary) Leaf Extract, Laminaria Digitata Extract, Zostera Marina Extract, Camellia Japonica Seed Oil, Sodium Carrageenan, Palmitoyl Tripeptide-1, Palmitoyl Tetrapeptide-7, Acetyl Hexapeptide-8, Sea Salt/Maris Sal/Sel Marin, Diatomaceous Earth, Silica, C12-20 Alkyl Gluoside, Xanthan Gum, Ethylhexylglycerin, Glucose, Sodium Hydroxide, Phospholipids, Sorbital, Disodium EDTA, Potassium Sorbate, Citric Acid, Sodium Benzoate, Lecithin, Caprylyl Glycol, Butylene Glycol, Disodium EDTA, Magnesium Ascorbyl Phosphate, Sorbic Acid, Glyceryl Caprylate, Sodium Metabisulfite, Carbomer, Sodium Lactate, Polysorbate 20, Phenoxyethanol, Parfum?Fragrance, Linalool

Questions? Comments?

Call 1-800-242-2284, M - F 9am - 5PM PST

H2O BEAUTY INFINITY+ product label

H2O+™

BEAUTY

INFINITY+

WRINKLE DELAY CREAM

SPF30

AGE DEFYING PEPTIDES + SUN PROTECTION

50 mL 1.7 U.S. Fl oz

WATER

We plus it up with energy, confidence, and advanced technology. The result is positively smart.

H2O + INFINITY+ WINKLE DELAY CREAM
SPF 30

PUMP THE BREAKS, WRINKLES l Put thise days of reckless sun-exposure behind you, leathery skin is so last year. The silky-texture of our Wrinkle Delay Cream with SPF 30 will quickly make you a believer. Featuring Camellia Japonica Oil and Red Algae extract, it protects against moisture loss and therefore helps ward off the appearance of wrinkles. Embrace the broad spectrum coverage and enjoy getting carded at the supermarket.

HOW TO USE
Massage on to face, neck, and chest every morning after cleansing and toning. Reapply every two hours. For best results, apply over your favorite H2O+ Beauty serum.

H2O+

Distributed by: H2O Plus, LLC

San Francisco, CA 94104

WWW.H2OPLUS.COM

2016 MADE IN THE USA

083-50123-001 50123